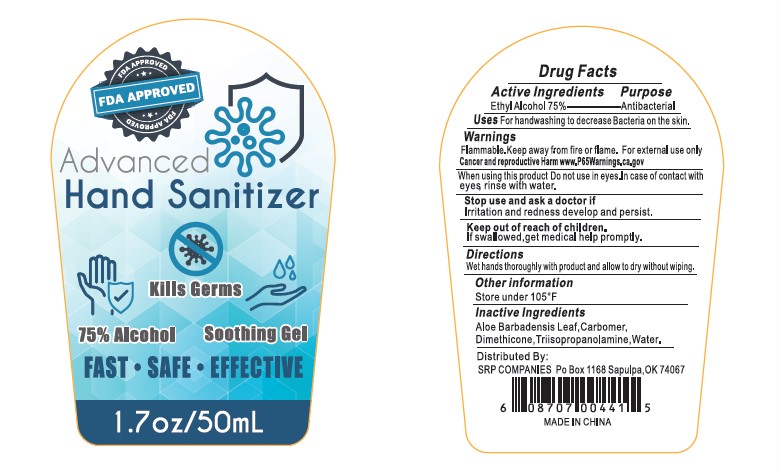 DRUG LABEL: Hand Sanitizer
NDC: 78048-001 | Form: GEL
Manufacturer: Dongguan City Dexu Toys Co.,Ltd
Category: otc | Type: HUMAN OTC DRUG LABEL
Date: 20200519

ACTIVE INGREDIENTS: ALCOHOL 75 mL/100 mL
INACTIVE INGREDIENTS: ALOE VERA LEAF; CARBOMER HOMOPOLYMER, UNSPECIFIED TYPE; WATER; TRIISOPROPANOLAMINE; DIMETHICONE

hand sanitizer

Active Ingredients

Ethyl Alcohol 75% Purpose: Antibactirial

Purpose

Antibacterial

Uses

for handwashing to decrease bacteria on the skin

Warnings

Flammable. Keep away from heat or flame.For external use only.

do not use in eyes.In case of contact with eye rinse with water

when using this product do not use in eyes.In case of contact with eye rinse with water

Stop use and ask a doctor if

irritation or redness develop and persist

Keep out of reach of children. If swallowed, get medical help promiptly

Directions

Wet hands thoroughly with product and allow to dry without wiping

Other information

Store under 105℉

Inactive ingredients

ALOE BARBADENSIS LEAF,carbomer,dimethicone,triisopropanolamine,water

Package Label - Principal Display Panel

50mL NDC: 78048-001-01